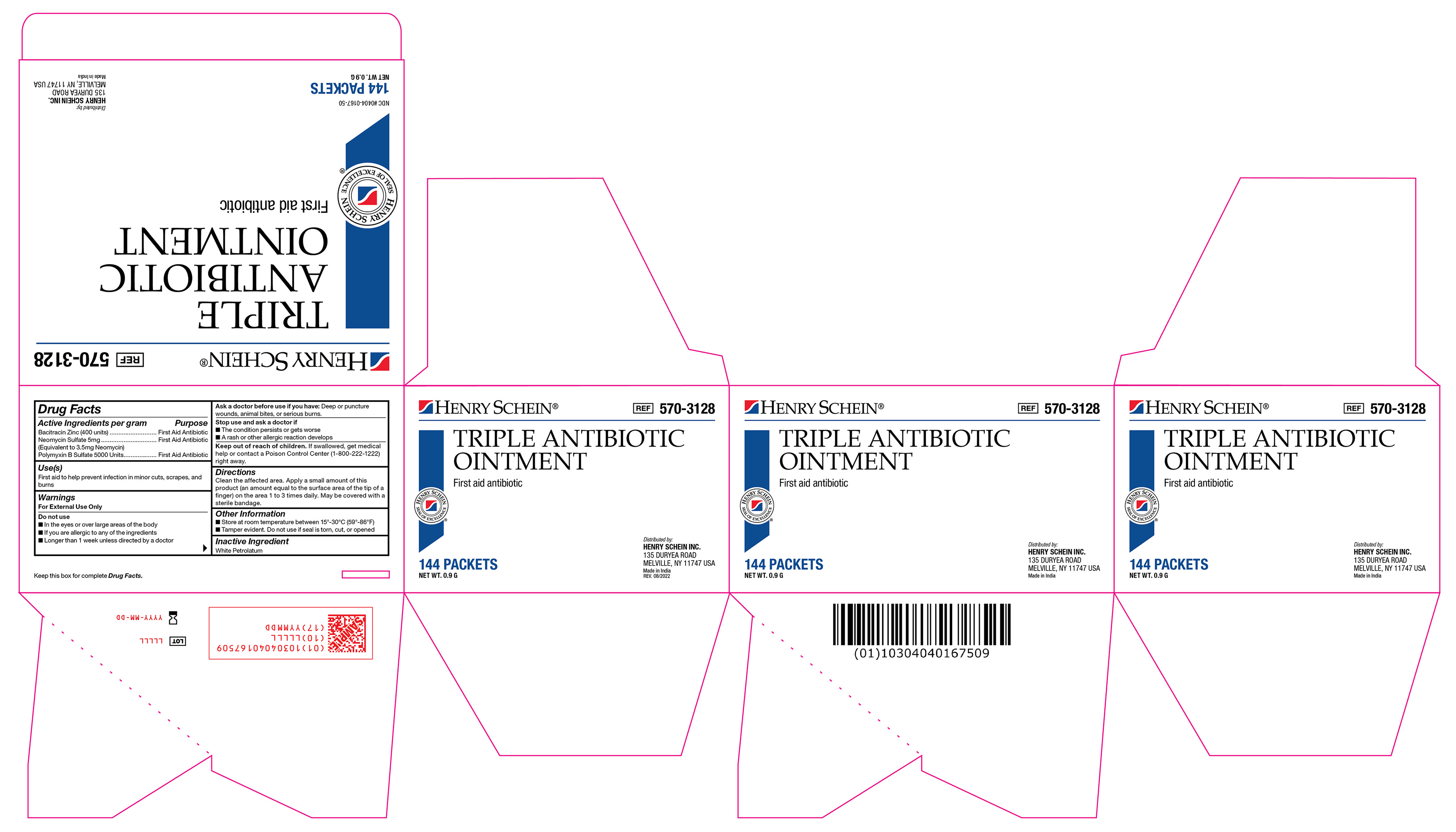 DRUG LABEL: Bacitracin Zinc, Neomycin Sulfate, and Polymyxin B Sulfate
NDC: 0404-0167 | Form: OINTMENT
Manufacturer: Henry Schein
Category: otc | Type: HUMAN OTC DRUG LABEL
Date: 20251125

ACTIVE INGREDIENTS: BACITRACIN ZINC 400 [iU]/1 g; NEOMYCIN SULFATE 5 mg/1 g; POLYMYXIN B SULFATE 5000 [iU]/1 g
INACTIVE INGREDIENTS: WHITE PETROLATUM

570-3128 Triple Antibiotic Ointment 0.9 g NDC 0404-0167-50

Active Ingredient

Bacitracin Zinc 400 units

Neomyxin Sulfate 5mg (Equivalent to 3.5mg Neomycin)

Polymyxin B Sulfate 5000 units

Purpose

First Aid Antibiotic

Uses

First aid to help prevent infection in minor cuts, scrapes, and burns

Warnings

For External Use Only

Do not use

• In the eyes or over large areas of the body

• If you are allergic to any of the ingredients

• Longer than 1 week unless directed by a doctor

Ask a doctor before use if you have

Deep or puncture wounds, animal bites, or serious burns

Stop use and ask a doctor if

• The condition persists or gets worse

• A rash or other allergic reaction develops

Keep out of reach of children

If swallowed, get medical help or contact a Poison Control Center (1-800-222-1222) right away.

Directions

Clean the affected area. Apply a small amount of this product (an amount equal to the surface area of the tip of a finger) on the area 1 to 3 times daily. May be covered with a sterile bandage.

Other Information

• Store at room temperature 15º-30ºC (59º-86°F)

• Tamper evident. Do not use if seal is torn, cut, or opened.

Inactive Ingredients

White Petrolatum

Label

Triple Antibiotic Label